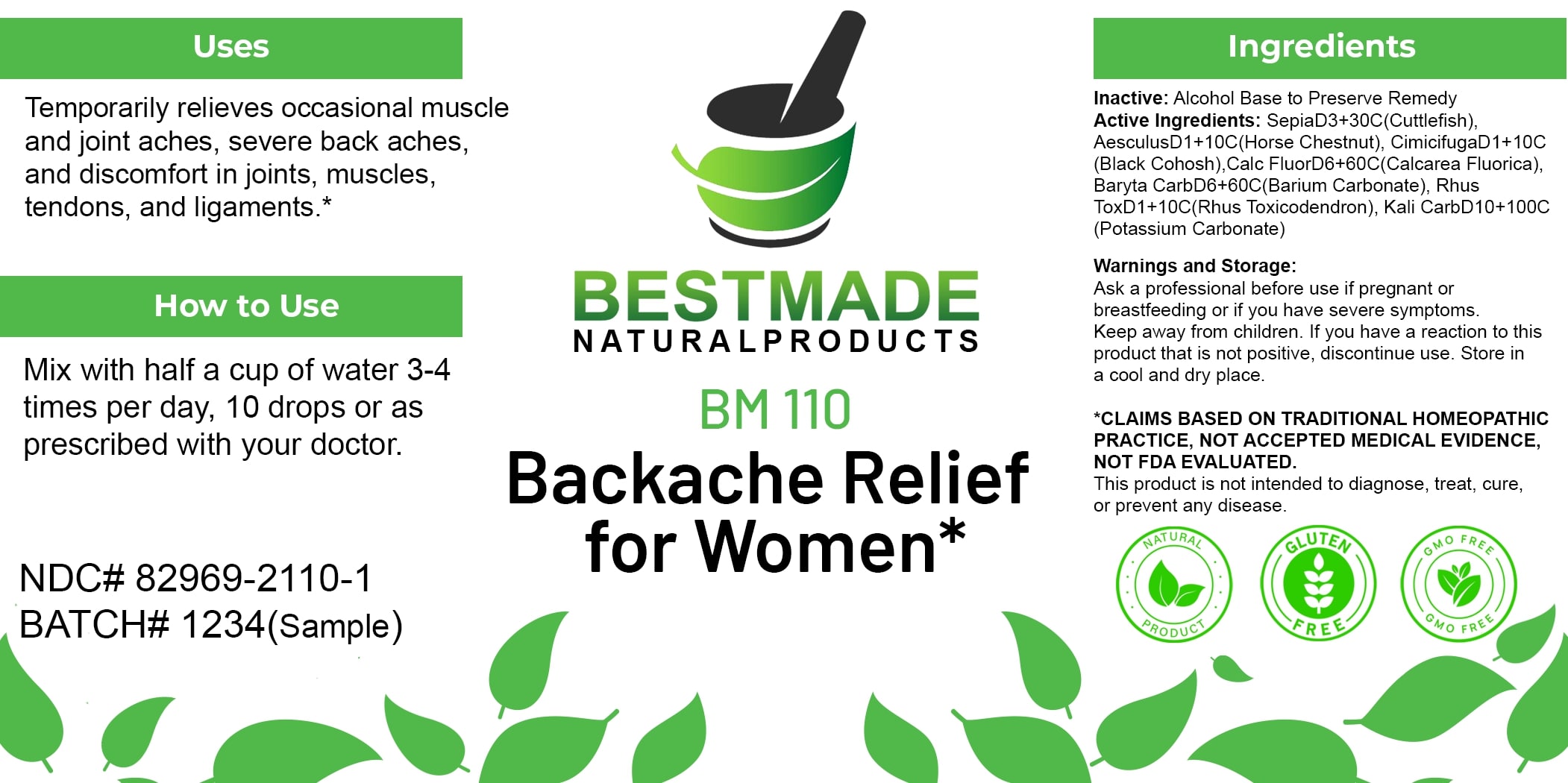 DRUG LABEL: Bestmade Natural Products BM110
NDC: 82969-2110 | Form: LIQUID
Manufacturer: Bestmade Natural Products
Category: homeopathic | Type: HUMAN OTC DRUG LABEL
Date: 20250207

ACTIVE INGREDIENTS: SEPIA OFFICINALIS JUICE 30 [hp_C]/30 [hp_C]; CALCIUM FLUORIDE 30 [hp_C]/30 [hp_C]; HORSE CHESTNUT 30 [hp_C]/30 [hp_C]; TOXICODENDRON PUBESCENS LEAF 30 [hp_C]/30 [hp_C]; POTASSIUM CARBONATE 30 [hp_C]/30 [hp_C]; CIMICIFUGA RACEMOSA ROOT 30 [hp_C]/30 [hp_C]; BARIUM CARBONATE 30 [hp_C]/30 [hp_C]
INACTIVE INGREDIENTS: ALCOHOL 30 [hp_C]/30 [hp_C]

BM110

DOSAGE AND ADMINISTRATION

How to Use

Mix with half a cup of water 3-4 times per day, 10 drops or as prescribed with your doctor.

INACTIVE INGREDIENT

Ingredients

Inactive: Alcohol Base to Preserve Remedy

ACTIVE INGREDIENT

Active Ingredients: SepiaD3+30C(Cuttlefish), AesculusD1+10C(Horse Chestnut), CimicifugaD1+10C (Black Cohosh), Calc FluorD6+60C(Calcarea Fluorica), Baryta CarbD6+60C(Barium Carbonate), Rhus ToxD1+10C(Rhus Toxicodendron), Kali CarbD10+100C (Potassium Carbonate)

Uses

Temporarily relieves occasional muscle and joint aches, severe back aches, and discomfort in joints, muscles, tendons, and ligaments.*

*CLAIMS BASED ON TRADITIONAL HOMEOPATHIC PRACTICE, NOT ACCEPTED MEDICAL EVIDENCE. NOT FDA EVALUATED.

This product is not intended to diagnose, treat, cure, or prevent any disease.

Uses

Temporarily relieves occasional muscle and joint aches, severe back aches, and discomfort in joints, muscles, tendons, and ligaments.*

*CLAIMS BASED ON TRADITIONAL HOMEOPATHIC PRACTICE, NOT ACCEPTED MEDICAL EVIDENCE. NOT FDA EVALUATED.

This product is not intended to diagnose, treat, cure, or prevent any disease.

KEEP OUT OF REACH OF CHILDREN

Warnings and Storage:

Ask a professional before use if pregnant or breastfeeding or if you have severe symptoms. Keep away from children. If you have a reaction to this product that is not positive, discontinue use. Store in a cool and dry place.

Warnings and Storage:

Ask a professional before use if pregnant or breastfeeding or if you have severe symptoms. Keep away from children. If you have a reaction to this product that is not positive, discontinue use. Store in a cool and dry place.

*CLAIMS BASED ON TRADITIONAL HOMEOPATHIC PRACTICE, NOT ACCEPTED MEDICAL EVIDENCE. NOT FDA EVALUATED.

This product is not intended to diagnose, treat, cure, or prevent any disease.

Entire package label